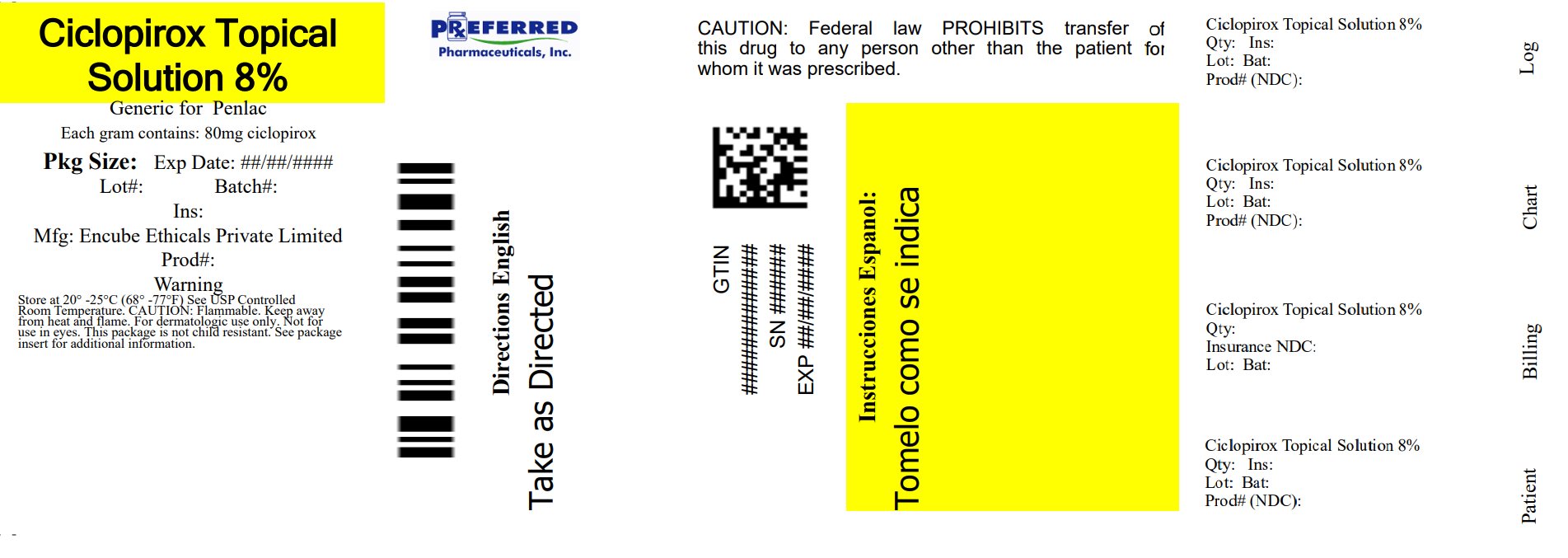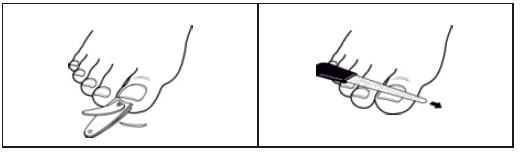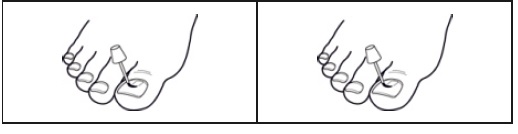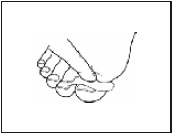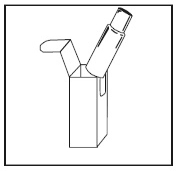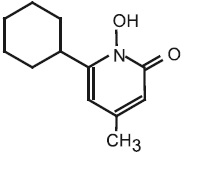 DRUG LABEL: CICLOPIROX
NDC: 68788-8755 | Form: SOLUTION
Manufacturer: Preferred Pharmaceuticals Inc.
Category: prescription | Type: HUMAN PRESCRIPTION DRUG LABEL
Date: 20260119

ACTIVE INGREDIENTS: CICLOPIROX 80 mg/1 mL
INACTIVE INGREDIENTS: ISOPROPYL ALCOHOL; ETHYL ACETATE; BUTYL ESTER OF METHYL VINYL ETHER/MALEIC ANHYDRIDE COPOLYMER (125000 MW)

Ciclopirox Topical Solution, 8% (Nail Lacquer)
Rx Only
For use on fingernails and toenails and immediately adjacent skin only
Not for use in eyes

DESCRIPTION

Ciclopirox topical solution, 8% (nail lacquer) contains a synthetic antifungal agent, ciclopirox. It is intended for topical use on fingernails and toenails and immediately adjacent skin.

Each gram of ciclopirox topical solution, 8% (nail lacquer) contains 80 mg ciclopirox in a solution base consisting of ethyl acetate, NF; isopropyl alcohol, USP; and butyl monoester of poly[methylvinyl ether/maleic acid] in isopropyl alcohol. Ethyl acetate and isopropyl alcohol are solvents that vaporize after application.

Ciclopirox topical solution, 8% (nail lacquer) is a clear, colorless to slightly yellowish solution.

The chemical name for ciclopirox is 6-cyclohexyl-1-hydroxy-4- methyl-2(1 H)-pyridone, with the empirical formula C12H17NO2 and a molecular weight of 207.27. The CAS Registry Number is [29342-05-0]. The chemical structure is:

CLINICAL PHARMACOLOGY

Microbiology
Mechanism of Action

The mechanism of action of ciclopirox has been investigated using various in vitro and in vivo infection models. One in vitro study suggested that ciclopirox acts by chelation of polyvalent cations (Fe^+3 or Al^+3) resulting in the inhibition of the metal-dependent enzymes that are responsible for the degradation of peroxides within the fungal cell. The clinical significance of this observation is not known.

Activity in vitro and ex vivo

In vitro methodologies employing various broth or solid media with and without additional nutrients have been utilized to determine ciclopirox minimum inhibitory concentration (MIC) values for the dermatophytic molds.(1-2) As a consequence, a broad range of MIC values, 1-20 μg/mL, were obtained for Trichophyton rubrum and Trichophyton mentagrophytes species. Correlation between in vitro MIC results and clinical outcome has yet to be established for ciclopirox.

One ex vivo study was conducted evaluating 8% ciclopirox against new and established Tricho phyton rubrum and Trichophyton mentagrophytes infections in ovine hoof material.(3) After 10 days of treatment the growth of T. rubrum and T. mentagrophytes in the established infection model was very minimally affected. Elimination of the molds from hoof material was not achieved in either the new or established infection models.

Susceptibility testing for Trichophyton rubrum species

In vitro susceptibility testing methods for determining ciclopirox MIC values against the dermatophytic molds, including Trichophyton rubrum species, have not been standardized or validated. Ciclopirox MIC values will vary depending on the susceptibility testing method employed, composition and pH of media and the utilization of nutritional supplements. Breakpoints to determine whether clinical isolates of Trichophyton rubrum are susceptible or resistant to ciclopirox have not been established.

Resistance

Studies have not been conducted to evaluate drug resistance development in T. rubrum species exposed to 8% ciclopirox topical solution. Studies assessing cross-resistance to ciclopirox and other known antifungal agents have not been performed.

Antifungal Drug Interactions

No studies have been conducted to determine whether ciclopirox might reduce the effectiveness of systemic antifungal agents for onychomycosis. Therefore, the concomitant use of 8% ciclopirox topical solution and systemic antifungal agents for onychomycosis is not recommended.

Pharmacokinetics

As demonstrated in pharmacokinetic studies in animals and man, ciclopirox olamine is rapidly absorbed after oral administration and completely eliminated in all species via feces and urine. Most of the compound is excreted either unchanged or as glucuronide. After oral administration of 10 mg of radiolabeled drug (14C-ciclopirox) to healthy volunteers, approximately 96% of the radioactivity was excreted renally within 12 hours of administration. Ninety-four percent of the renally excreted radioactivity was in the form of glucuronides. Thus, glucuronidation is the main metabolic pathway of this compound.

Systemic absorption of ciclopirox was determined in 5 patients with dermatophytic onychomycoses, after application of ciclopirox topical solution, 8% (nail lacquer), to all 20 digits and adjacent 5 mm of skin once daily for six months. Random serum concentrations and 24 hour urinary excretion of ciclopirox were determined at two weeks and at 1, 2, 4 and 6 months after initiation of treatment and 4 weeks post-treatment. In this study, ciclopirox serum levels ranged from 12-80 ng/mL. Based on urinary data, mean absorption of ciclopirox from the dosage form was <5% of the applied dose. One month after cessation of treatment, serum and urine levels of ciclopirox were below the limit of detection.

In two vehicle-controlled trials, patients applied ciclopirox topical solution, 8% (nail lacquer) to all toenails and affected fingernails. Out of a total of 66 randomly selected patients on active treatment, 24 had detectable serum ciclopirox concentrations at some point during the dosing interval (range 10.0-24.6 ng/mL). It should be noted that eleven of these 24 patients took concomitant medication containing ciclopirox as ciclopirox olamine (Loprox® Cream, 0. 77%).

The penetration of the ciclopirox topical solution, 8% (nail lacquer), was evaluated in an in vitro investigation. Radiolabeled ciclopirox applied once to onychomycotic toenails that were avulsed demonstrated penetration up to a depth of approximately 0.4 mm. As expected, nail plate concentrations decreased as a function of nail depth. The clinical significance of these findings in nail plates is unknown. Nail bed concentrations were not determined.

INDICATIONS AND USAGE

(To understand fully the indication for this product, please read the entire INDICATIONS AND USAGE section of thelabeling.)

Ciclopirox topical solution, 8% (nail lacquer), as a component of a comprehensive management program, is indicated as topical treatment in immunocompetent patients with mild to moderate onychomycosis of fingernails and toenails without lunula involvement, due to Trichophyton rubrum. The comprehensive management program includes removal of the unattached, infected nails as frequently as monthly, by a health care professional who has special competence in the diagnosis and treatment of nail disorders, including minor nail procedures.

- No studies have been conducted to determine whether ciclopirox might reduce the effectiveness of systemic antifungal agents for onychomycosis. Therefore, the concomitant use of ciclopirox topical solution, 8% (nail lacquer) and systemic antifungal agents for onychomycosis, is not recommended.
- Ciclopirox topical solution, 8% (nail lacquer), should be used only under medical supervision as described above.
- The effectiveness and safety of ciclopirox topical solution, 8% (nail lacquer), in the following populations has not been studied. The clinical trials with use of ciclopirox topical solution, 8% (nail lacquer), excluded patients who: were pregnant or nursing, planned to become pregnant, had a history of immunosuppression (e.g., extensive, persistent, or unusual distribution of dermatomycoses, extensive seborrheic dermatitis, recent or recurring herpes zoster, or persistent herpes simplex), were HIV seropositive, received organ transplant, required medication to control epilepsy, were insulin dependent diabetics or had diabetic neuropathy. Patients with severe plantar (moccasin) tinea pedis were also excluded.
- The safety and efficacy of using ciclopirox topical solution, 8% (nail lacquer), daily for greater than 48 weeks have not been established.

Clinical Trials Data

The results of use of ciclopirox topical solution, 8% (nail lacquer), in treatment of onychomycosis of the toenail without lunula involvement were obtained from two double-blind, placebo-controlled studies conducted in the US. In these studies, patients with onychomycosis of the great toenails without lunula involvement were treated with ciclopirox topical solution, 8% (nail lacquer), in conjunction with monthly removal of the unattached, infected toenail by the investigator. Ciclopirox topical solution, 8% (nail lacquer), was applied for 48 weeks. At baseline, patients had 20-65% involvement of the target great toenail plate. Statistical significance was demonstrated in one of two studies for the endpoint “complete cure” (clear nail and negative mycology), and in two studies for the endpoint “almost clear” (<10% nail involvement and negative mycology) at the end of study. These results are presented below.

At Week 48 (plus Last Observation Carried Forward) for the Intent-to-Treat (ITT) Population
 | Study 312 |  | Study 313
 | Active | Vehicle | Active | Vehicle
Complete Cure* | 6/110 (5.5%) | 1/109 (0.9%) | 10/118 (8.5%) | 0/117 (0%)
Almost Clear** | 7/107 (6.5%) | 1/108 (0.9%) | 14/116 (12%) | 1/115 (0.9%)
Negative Mycology Alone*** | 30/105 (29%) | 12/106 (11%) | 41/115 (36%) | 10/114 (9%)
* Clear nail and negative mycology
** ≤10% nail involvement and negative mycology
*** Negative KOH and negative culture

The summary of reported patient outcomes for the ITT population at 12 weeks following the end of treatment are presented below. Note that post - treatment efficacy assessments were scheduled only for patients who achieved a complete cure.

Post-treatment Week 12 Data for Patients Who Achieved Complete Cure at Week 48
 | Study 312 |  | Study 313
 | Active | Vehicle | Active | Vehicle
Number of Treated Patients | 112 | 111 | 119 | 118
Complete Cure at Week 48 | 6 | 1 | 10 | 0
Post-treatment Week 12 Outcomes: Patients Missing All Week 12 Assessments Patients with Week 12 Assessments Complete Cure Almost Clear Negative Mycology | 2 4 3 2* 3 | 0 1 1 1 1 | 2 8 4 1* 5 | 0 0 0 0 0

*Four patients (from studies 312 and 313) who were completely cured did not have post-treatment Week 12 planimetry data.

CONTRAINDICATIONS

Ciclopirox topical solution, 8% (nail lacquer), is contraindicated in individuals who have shown hypersensitivity to any of its components.

WARNINGS

Ciclopirox topical solution, 8% (nail lacquer), is not for ophthalmic, oral, or intravaginal use. For use on nails and immediately adjacent skin only.

PRECAUTIONS

If a reaction suggesting sensitivity or chemical irritation should occur with the use of ciclopirox topical solution, 8% (nail lacquer), treatment should be discontinued and appropriate therapy instituted.

So far there is no relevant clinical experience with patients with insulin dependent diabetes or who have diabetic neuropathy. The risk of removal of the unattached, infected nail, by the health care professional and trimming by the patient should be carefully considered before prescribing to patients with a history of insulin dependent diabetes mellitus or diabetic neuropathy.

Information for Patients

Patients should have detailed instructions regarding the use of ciclopirox topical solution, 8% (nail lacquer), as a component of a comprehensive management program for onychomycosis in order to achieve maximum benefit with the use of this product.

The patient should be told to:

1. Use ciclopirox topical solution, 8% (nail lacquer), as directed by a health care professional. Avoid contact with the eyes and mucous membranes. Contact with skin other than skin immediately surrounding the treated nail(s) should be avoided. Ciclopirox topical solution, 8% (nail lacquer), is for external use only.

2. Ciclopirox topical solution, 8% (nail lacquer), should be applied evenly over the entire nail plate and 5 mm of surrounding skin. If possible, ciclopirox topical solution, 8% (nail lacquer), should be applied to the nail bed, hyponychium, and the under surface of the nail plate when it is free of the nail bed (e.g., onycholysis). Contact with the surrounding skin may produce mild, transient irritation (redness).

3. Removal of the unattached, infected nail, as frequently as monthly, by a health care professional is needed with use of this medication. Inform a health care professional if they have diabetes or problems with numbness in your toes or fingers for consideration of the appropriate nail management program.

4. Inform a health care professional if the area of application shows signs of increased irritation (redness, itching, burning, blistering, swelling, oozing).

5. Up to 48 weeks of daily applications with ciclopirox topical solution, 8% (nail lacquer), and professional removal of the unattached, infected nail, as frequently as monthly, are considered the full treatment needed to achieve a clear or almost clear nail (defined as 10% or less residual nail involvement).

6. Six months of therapy with professional removal of the unattached, infected nail may be required before initial improvement of symptoms is noticed.

7. A completely clear nail may not be achieved with use of this medication. In clinical studies less than 12% of patients were able to achieve either a completely clear or almost clear toenail.

8. Do not use the medication for any disorder other than that for which itis prescribed.

9. Do not use nail polish or other nail cosmetic products on the treated nails.

10. Avoid use near heat or open flame, because product is flammable.

Carcinogenesis, Mutagenesis, Impairment of Fertility

No carcinogenicity study was conducted with ciclopirox topical solution, 8% (nail lacquer), formulation. A carcinogenicity study of ciclopirox (1% and 5% solutions in polyethylene glycol 400) in female mice dosed topically twice per week for 50 weeks followed by a 6- month drug-free observation period prior to necropsy revealed no evidence of tumors at the application sites.

In human systemic tolerability studies following daily. application (~340 mg of ciclopirox topical solution, 8% (nail lacquer)), in subjects with distal subungual onychomycosis, the average maximal serum level of ciclopirox was 31±28 ng/mL after two months of once daily applications. This level was 159 times lower than the lowest toxic dose and 115 times lower than the highest nontoxic dose in rats and dogs fed 7.7 and 23.1 mg ciclopirox (as ciclopirox olamine)/kg/day.

The following in vitro genotoxicity tests have been conducted with ciclopirox: evaluation of gene mutation in Ames Salmonella and E. coli assays (negative): chromosome aberration assays in V79 Chinese hamster lung fibroblasts, with and without metabolic activation (positive); gene mutation assay in the HGPRT-test with V79 Chinese hamster lung fibroblasts (negative); unscheduled DNA synthesis in human A549 cells (negative); and BALB/c3T3 cell transformation assay (negative). In an in vivoChinese hamster bone marrow cytogenetic assay, ciclopirox was negative for chromosome aberrations at 5,000 mg/kg.

The following in vitro genotoxicity tests were conducted with ciclopirox topical solution, 8% (nail lacquer): Ames Salmonella test (negative); unscheduled DNA synthesis in the rat hepatocytes (negative); cell transformation assay in BALB/c3T3 cell assay (positive). The positive response of the lacquer formulation in the BALB/c3T3 test was attributed to its butyl monoester of poly [methylvinyl ether/maleic acid] resin component (Gantrez® ES-435), which also tested positive in this test. The cell transformation assay may have been confounded because of the film-forming nature of the resin. Gantrez® ES-435 tested nonmutagenic in both the in vitro mouse lymphoma forward mutation assay with or without activation and unscheduled DNA, synthesis assay in rat hepatocytes.

Oral reproduction studies in rats at doses up to 3.85 mg ciclopirox (as ciclopirox olamine)/kg/day [equivalent to approximately 1.4 times the potential exposure at the maximum recommended human topical dose (MRHTD)] did not reveal any specific effects on fertility or other reproductive parameters. MRHTD (mg/m2) is based on the assumption of 100% systemic absorption of 27.12 mg ciclopirox (~340 mg ciclopirox topical solution, 8% (nail lacquer)), that will cover all the fingernails and toenails including 5 mm proximal and lateral fold area plus onycholysis to a maximal extent of 50%.

Pregnancy

Teratogenic effects: Pregnancy Category B

Teratology studies in mice, rats, rabbits, and monkeys at oral doses of up to 77, 23, 23, or 38.5 mg, respectively, of ciclopirox as ciclopirox olamine/kg/day (14, 8, 17, and 28 times MRHTD), or in rats and rabbits receiving topical doses of up to 92.4 and 77 mg/kg/day, respectively (33 and 55 times MRHTD), did not indicate any significant fetal malformations.

There are no adequate or well-controlled studies of topically applied ciclopirox in pregnant women. Ciclopirox topical solution, 8% (nail lacquer), should be used during pregnancy only if the potential benefit justifies the potential risk to the fetus.

Nursing Mothers

It is not known whether this drug is excreted in human milk. Since many drugs are excreted in human milk, caution should be exercised when ciclopirox topical solution, 8% (nail lacquer), is administered to a nursing woman.

Pediatric Use

Based on the safety profile in adults, ciclopirox topical solution, 8% (nail lacquer), is considered safe for use in children twelve years and older. No clinical trials have been conducted in the pediatric population.

Geriatric Use

Clinical studies of ciclopirox topical solution, 8% (nail lacquer), did not include sufficient numbers of subjects aged 65 and over to determine whether they respond differently from younger subjects. Other reported clinical experience has not identified differences in responses between elderly and younger patients.

ADVERSE REACTIONS

In the vehicle-controlled clinical trials conducted in the US, 9% (30/327) of patients treated with ciclopirox topical solution, 8% (nail lacquer), and 7% (23/328) of patients treated with vehicle reported treatment-emergent adverse events (TEAE) considered by the investigator to be causally related to the test material. The incidence of these adverse events, within each body system, was similar between the treatment groups except for Skin and Appendages: 8% (27/327) and 4% (14/328) of subjects in the ciclopirox and vehicle groups reported at least one adverse event, respectively. The most common were rash-related adverse events: periungual erythema and erythema of the proximal nail fold were reported more frequently in patients treated with ciclopirox topical solution, 8% (nail lacquer), (5% [16/327]) than in patients treated with vehicle (1% [3/328]). Other TEAEs thought to be causally related included nail disorders such as shape change, irritation, ingrown toenail, and discoloration.

The incidence of nail disorders was similar between the treatment groups (2% [6/327] in the ciclopirox topical solution, 8% (nail lacquer), group and 2% [7/328] in the vehicle group). Moreover, application site reactions and/or burning of the skin occurred in 1 % of patients treated with ciclopirox topical solution, 8% (nail lacquer), (3/327) and vehicle (4/328).

A21-Day Cumulative Irritancy study was conducted under conditions of semi-occlusion. Mild reactions were seen in 46% of patients with the ciclopirox topical solution, 8% (nail lacquer), 32% with the vehicle and 2% with the negative control, but all were reactions of mild transient erythema. There was no evidence of allergic contact sensitization for either the ciclopirox topical solution, 8% (nail lacquer), or the vehicle base. In a separate study of the photosensitization potential of ciclopirox topical solution, 8% (nail lacquer), in a maximized test design that included the occluded application of sodium lauryl sulfate, no photoallergic reactions were noted. In four subjects localized allergic contact reactions were observed. In the vehicle-controlled studies, one patient treated with ciclopirox topical solution, 8% (nail lacquer), discontinued treatment due to a rash, localized to the palm (causal relation to test material undetermined).

Use of ciclopirox topical solution, 8% (nail lacquer), for 48 additional weeks was evaluated in an open-label extension study conducted in patients previously treated in the vehicle-controlled studies. Three percent (9/281) of subjects treated with ciclopirox topical solution, 8% (nail lacquer), experienced at least one TEAE that the investigator thought was causally related to the test material. Mild rash in the form of periungual erythema (1% [2/281]) and nail disorders (1 % [4/281]) were the most frequently reported. Four patients discontinued because of TEAEs. Two of the four had events considered to be related to test material: one patient’s great toenail “broke away” and another had an elevated creatine phosphokinase level on Day 1 (after 48 weeks of treatment with vehicle in the previous vehicle-controlled study).

DOSAGE AND ADMINISTRATION

Ciclopirox topical solution, 8% (nail lacquer), should be used as a component of a comprehensive management program for onychomycosis. Removal of the unattached, infected nail, as frequently as monthly, by a health care professional, weekly trimming by the patient, and daily application of the medication are all integral parts of this therapy. Careful consideration of the appropriate nail management program should be given to patients with diabetes (see PRECAUTIONS).

Nail Care By Health Care Professionals

Removal of the unattached, infected nail, as frequently as monthly, trimming of onycholytic nail, and filing of excess horny material should be performed by professionals trained in treatment of nail disorders.

Nail Care By Patient

Patients should file away (with emery board) loose nail material and trim nails, as required, or as directed by the health care professional, every seven days after ciclopirox topical solution, 8% (nail lacquer), is removed with alcohol.

Ciclopirox topical solution, 8% (nail lacquer), should be applied once daily (preferably at bedtime or eight hours before washing) to all affected nails with the applicator brush provided. The ciclopirox topical solution, 8% (nail lacquer), should be applied evenly over the entire nail plate.

If possible, ciclopirox topical solution, 8% (nail lacquer), should be applied to the nail bed, hyponychium, and the under surface of the nail plate when it is free of the nail bed (e.g., onycholysis).

The ciclopirox topical solution, 8% (nail lacquer), should not be removed on a daily basis. Daily applications should be made over the previous coat and removed with alcohol every seven days. This cycle should be repeated throughout the duration of therapy.

HOW SUPPLIED

Ciclopirox topical solution, 8% (nail lacquer), is supplied in 6.6 mL (NDC 68788-8755-6) glass bottles with screw caps which are fitted with brushes.

Protect from light (e.g., store the bottle in the carton after every use).

Ciclopirox topical solution, 8% (nail lacquer), should be stored at 20°C to 25°C (68°F to 77°F) [see USP Controlled Room Temperature.]

CAUTION: Flammable. Keep away from heat and flame.

Rx ONLY

To report SUSPECTED ADVERSE REACTIONS, contact Encube Ethicals Private Limited at 1-833-285-4151 and/or FDA at 1-800-FDA-1088 or www.fda.gov/medwatch.

Made in Finland

Manufactured by: Encube Ethicals Pvt. Ltd.
Plot No. C-1, Madkaim Industrial Estate,
Madkaim, Post: Mardol, Panda, Goa-403404, India.

References:
1. Dittmar W., Lohaus G. 1973. HOE296, A new antimycotic compound with a broad antimicrobial spectrum. Arzneim-Forsch./ Drug Res. 23:670-674.
2. Niewerth et. al., 1998. Antimicrobial susceptibility testing of dermatophytes: Comparison of the agar macrodilution and broth micro dilution tests. Chemotherapy. 44:31-35.
3. Yang et. al. 1997. A new simulation model for studying in vitro topical penetration of antifungal drugs into hard keratin. J. Mycol. Med. 7:195-98.

Gantrez is a registered trademark of GAF Corporation

Rev. 01/25

Relabeled By: Preferred Pharmaceuticals Inc.

Patient Information and Instructions

Ciclopirox Topical Solution, 8% (Nail Lacquer)

Patient Information and Instructions

Patients should have detailed instructions regarding the use of ciclopirox topical solution, 8% (nail lacquer), as a component of a comprehensive management program for onychomycosis in order to achieve maximum benefit with the use of this product. Discuss your treatment plan with your health care professional for regular removal of the unattached, infected nail.

Before using this medication, tell your doctor if you:

- Are pregnant or nursing
- Are an insulin dependent diabetic or have diabetic neuropathy
- Have a history of immunosuppression
- Are immunocompromised (e.g., received an organ transplant, etc.)
- Require medication to control epilepsy
- Use or require topical corticosteroids on a repeated monthly basis
- Use steroid inhalers on a regular basis

Patient Information:

- Use ciclopirox topical solution, 8% (nail lacquer), as directed by your health care professional.
- Ciclopirox topical solution, 8% (nail lacquer), is for external use only.
- Contact with skin other than skin immediately surrounding the treated nail(s)should be avoided.
- Avoid contact with the eyes and mucous membranes.
- Removal of the unattached, infected nail, as frequently as monthly, by your health care professional is needed with use of this medication to obtain maximal benefit with use of this product. If you have diabetes or problems with numbness in your toes or fingers, talk to your health care provider before trimming your nails or removing any nail material.
- Inform your health care professional if the area of application shows signs of increased irritation (redness, itching, burning, blistering, swelling, oozing).
- Up to 48 weeks of daily applications with ciclopirox topical solution, 8% (nail lacquer), and professional removal, as frequently as monthly, of the unattached, infected nail are considered the full treatment time to achieve a clear or almost clear nail (defined as 10% or less residual nail involvement). Six months of therapy with professional removal of the unattached, infected nail may be required before initial improvement of symptoms is noticed.
- A completely clear nail may not be achieved with use of this medication. In clinical studies less than 12% of patients were able to achieve either a clear or almost clear toenail."
- Do not use nail polish or other nail cosmetic products on the treated nails.
- Avoid use near heat or open flame, because product is flammable.

Patient Instructions

1. Before starting treatment, remove any loose nail or nail material using nail clippers or nail files. If you have diabetes or problems with numbness in your toes or fingers, talk to your health care provider before trimming your nails or removing any nail material.

2. Apply Ciclopirox topical solution, 8% (nail lacquer), once daily (preferably at bedtime) to all affected nails with the applicator brush provided. Apply the lacquer evenly over the entire nail. Where possible, nail lacquer should also be applied to the underside of the nail and to the skin beneath it. Allow lacquer to dry (approximately 30 seconds) before putting on socks or stockings. After applying medication, wait 8 hours before taking a bath or shower.

3. Apply Ciclopirox topical solution, 8% (nail lacquer), daily over the previous coat.

4. Once a week, remove the Ciclopirox topical solution, 8% (nail lacquer), with alcohol. Remove as much as possible of the damaged nail using scissors, nail clippers, or nail files.

5. Repeat process (steps 2 through 4).

Please Note:

1. To prevent screw cap from sticking to the bottle, do not allow solution to get into the bottle threads.

2. To prevent the solution from drying out, bottle should be closed tightly after every use.
3. To protect from light, replace bottle into carton after each use.

Made in Finland

Manufactured by:

Encube Ethicals Pvt. Ltd.
Plot No. C-1, Madkaim Industrial Estate,
Madkaim, Post: Mardol, Panda,
Goa-403404, India.

Distributed by:
Encube Ethicals, Inc.
200 Meredith Drive, Suite 202
Durham, NC 27713 USA

Rev. 01/25

Relabeled By: Preferred Pharmaceuticals Inc.

PACKAGE LABEL.PRINCIPAL DISPLAY PANEL

Rx Only

NDC 68788-8755-6

Ciclopirox Topical Solution 8% (Nail Lacquer)

For Dermatologic Use Only

Not for Use in Eyes

One 6.6 mL Bottle